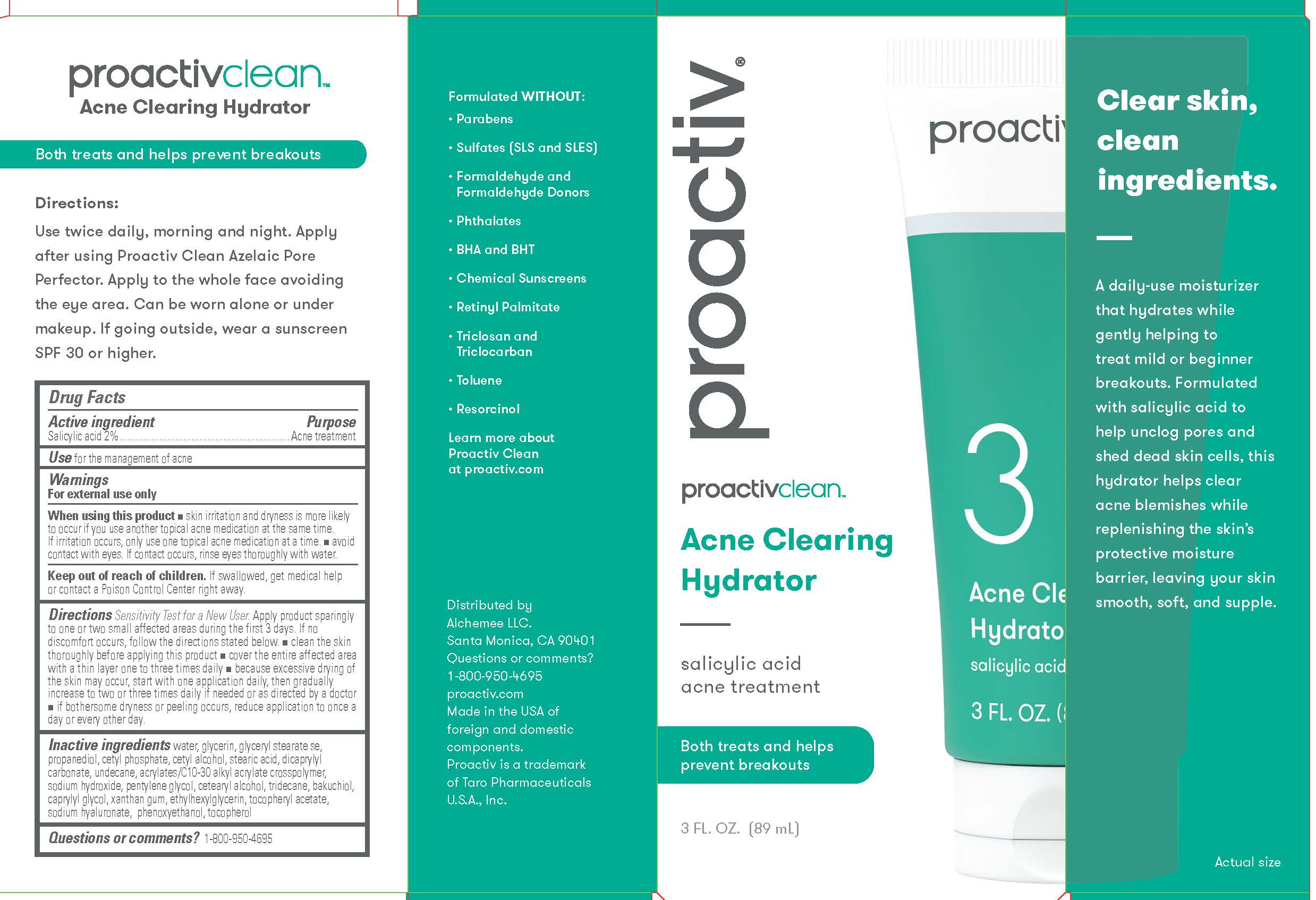 DRUG LABEL: Proactiv Clean Acne Clearing Hydrator
NDC: 11410-458 | Form: GEL
Manufacturer: Alchemee, LLC
Category: otc | Type: HUMAN OTC DRUG LABEL
Date: 20260107

ACTIVE INGREDIENTS: SALICYLIC ACID 2 mg/100 mL
INACTIVE INGREDIENTS: WATER; GLYCERIN; PROPANEDIOL; CETYL PHOSPHATE; CETYL ALCOHOL; STEARIC ACID; DICAPRYLYL CARBONATE; UNDECANE; CARBOMER INTERPOLYMER TYPE A (ALLYL SUCROSE CROSSLINKED); PENTYLENE GLYCOL; CETOSTEARYL ALCOHOL; TRIDECANE; BAKUCHIOL; GLYCERYL MONOSTEARATE; CAPRYLYL GLYCOL; XANTHAN GUM; ETHYLHEXYLGLYCERIN; .ALPHA.-TOCOPHEROL ACETATE; HYALURONATE SODIUM; TOCOPHEROL; SODIUM HYDROXIDE; PHENOXYETHANOL

Proactiv Clean Acne Clearing Hydrator

Drug Facts

Active ingredient

Salicylic Acid 2%

Purpose

Acne treatment

Use

for the management of acne

Warnings

For external use only

When using this product

- skin irritation and dryness is more likely to occur if you use another topical acne medication at the same time. If irritation occurs, only use one topical acne medication at a time.
- avoid contact with eyes. If contact occurs, rinse eyes thoroughly with water.

Keep out of reach of children.

If swallowed, get medical help or contact a Poison Control Center right away.

Directions

- Sensitivity Test for a New User. Apply product sparingly to one or two small affected areas during the first 3 days. If no discomfort occurs, follow the directions stated below.
- clean the skin thoroughly before applying this product
- cover the entire affected area with a thin layer one to three times daily
- because excessive drying of the skin may occur, start with one application daily, then gradually increase to two or three times daily if needed or as directed by a doctor
- if bothersome dryness or peeling occurs, reduce application to once a day or every other day.

Inactive ingredients

Water, Glycerin, Glyceryl Stearate SE, Propanediol, Cetyl Phosphate, Cetyl Alcohol, Stearic Acid, Dicaprylyl Carbonate, Undecane, Acrylates/C10-30 Alkyl Acrylate Crosspolymer, Sodium Hydroxide, Pentylene Glycol, Cetearyl Alcohol, Tridecane, Bakuchiol, Caprylyl Glycol, Xanthan Gum, Ethylhexylglycerin, Tocopheryl Acetate, Sodium Hyaluronate, Phenoxyethanol, Tocopherol

Questions or comments?

1-800-950-4695

Distributed by
Alchemee LLC.
Santa Monica, CA 90401
Questions or comments?
1-800-950-4695
proactiv.com
Made in the USA of
foreign and domestic
components.
Proactiv is a trademark of
Taro Pharmaceuticals
U.S.A., Inc.

PRINCIPAL DISPLAY PANEL - 3 FL. OZ. (89 mL)

proactiv®

proactivcleanTM
Acne Clearing
Hydrator

3 FL. OZ. (89 mL)

salicylic acid
acne treatment